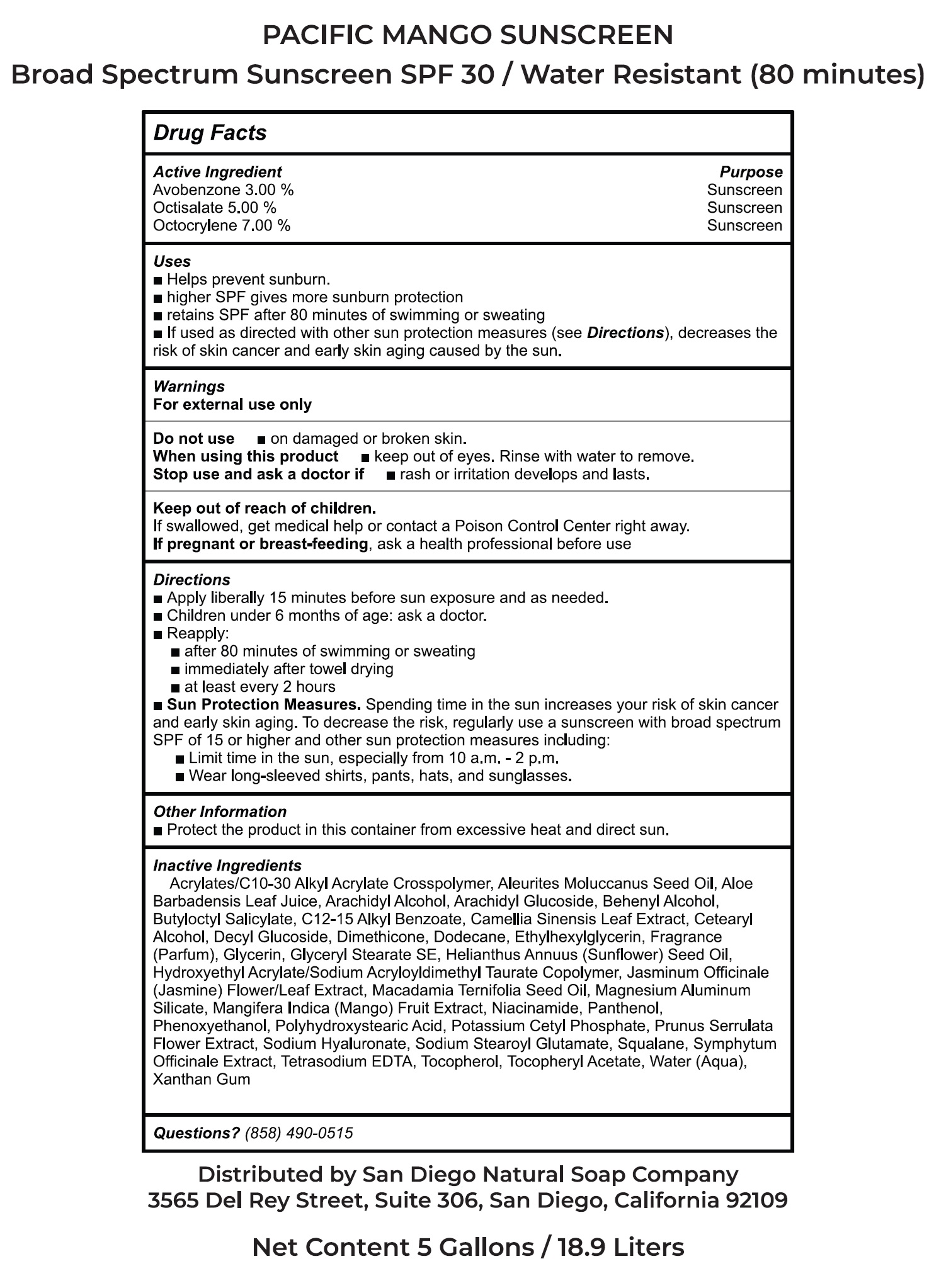 DRUG LABEL: Pacific Mango Sunscreen SPF 30
NDC: 85217-584 | Form: CREAM
Manufacturer: SAN DIEGO NATURAL SOAP COMPANY
Category: otc | Type: HUMAN OTC DRUG LABEL
Date: 20250206

ACTIVE INGREDIENTS: AVOBENZONE 30 mg/0.001 L; OCTISALATE 50 mg/0.001 L; OCTOCRYLENE 70 mg/0.001 L
INACTIVE INGREDIENTS: KUKUI NUT OIL; ALOE VERA LEAF; ARACHIDYL ALCOHOL; ARACHIDYL GLUCOSIDE; BEHENYL ALCOHOL; BUTYLOCTYL SALICYLATE; ALKYL (C12-15) BENZOATE; GREEN TEA LEAF; CETEARYL ALCOHOL; DECYL GLUCOSIDE; DIMETHICONE, UNSPECIFIED; DODECANE; ETHYLHEXYLGLYCERIN; GLYCERIN; GLYCERYL STEARATE SE; SUNFLOWER OIL; JASMINUM OFFICINALE FLOWER; MACADAMIA TERNIFOLIA SEED OIL; MAGNESIUM ALUMINUM SILICATE; MANGO; NIACINAMIDE; PANTHENOL; PHENOXYETHANOL; POTASSIUM CETYL PHOSPHATE; PRUNUS SERRULATA FLOWER; HYALURONATE SODIUM; SODIUM STEAROYL GLUTAMATE; SQUALANE; EDETATE SODIUM; TOCOPHEROL; .ALPHA.-TOCOPHEROL ACETATE; WATER; XANTHAN GUM

Pacific Mango Sunscreen SPF 30

Active Ingredient

Avobenzone 3.00%

Octisalate 5.00%

Octocrylene 7.00%

Purpose

Sunscreen

Uses

- Helps prevent sunburn.
- higher SPF gives more sunburn protection
- retains SPF after 80 minutes of swimming or sweating
- If used as directed with other sun protection measures (see Directions), decreases the risk of skin cancer and early skin aging caused by the sun.

Warnings

For external use only

Do not use

- on damaged or broken skin.

When using this product

- keep out of eyes. Rinse with water to remove.

Stop use and ask a doctor if

- rash or irritation develops and lasts.

Keep out of reach of children.

If swallowed, get medical help or contact a Poison Control Center right away.

If pregnant or breast-feeding,

ask a health professional before use

Directions

- Apply liberally 15 minutes before sun exposure and as needed.
- Children under 6 months of age: ask a doctor.
- Reapply:
- after 80 minutes of swimming or sweating
- immediately after towel drying
- at least every 2 hours
- Sun Protection Measures.Spending time in the sun increases your risk of skin cancer and early skin aging. To decrease the risk, regularly use a sunscreen with broad spectrum SPF of 15 or higher and other sun protection measures including:
- Limit time in the sun, especially from 10 a.m. - 2 p.m.
- Wear long-sleeved shirts, pants, hats, and sunglasses.

Other Information

- Protect the product in this container from excessive heat and direct sun.

Inactive Ingredients

Acrylates/C10-30 Alkyl Acrylate Crosspolymer, Aleurites Moluccanus Seed Oil, Aloe Barbadensis Leaf Juice, Arachidyl Alcohol, Arachidyl Glucoside, Behenyl Alcohol, Butyloctyl Salicylate, C12-15 Alkyl Benzoate, Camellia Sinensis Leaf Extract, Cetearyl Alcohol, Decyl Glucoside, Dimethicone, Dodecane, Ethylhexylglycerin, Fragrance (Parfum), Glycerin, Glyceryl Stearate SE, Helianthus Annuus (Sunflower) Seed Oil, Hydroxyethyl Acrylate/Sodium Acryloyldimethyl Taurate Copolymer, Jasminum Officinale (Jasmine) Flower/Leaf Extract, Macadamia Ternifolia Seed Oil, Magnesium Aluminum Silicate, Mangifera Indica (Mango) Fruit Extract, Niacinamide, Panthenol, Phenoxyethanol, Polyhydroxystearic Acid, Potassium Cetyl Phosphate, Prunus Serrulata Flower Extract, Sodium Hyaluronate, Sodium Stearoyl Glutamate, Squalane, Symphytum Officinale Extract, Tetrasodium EDTA, Tocopherol, Tocopheryl Acetate, Water (Aqua), Xanthan Gum

Questions?

(858) 490-0515